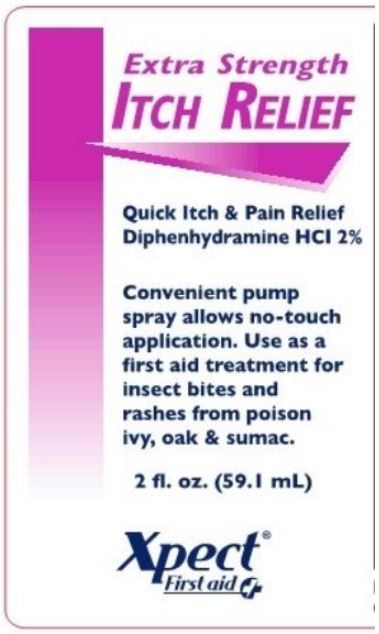 DRUG LABEL: Xpect Extra Strength Itch Relief
NDC: 42961-218 | Form: SPRAY
Manufacturer: Cintas Corporation
Category: otc | Type: HUMAN OTC DRUG LABEL
Date: 20250924

ACTIVE INGREDIENTS: DIPHENHYDRAMINE HYDROCHLORIDE 2 mg/100 mL
INACTIVE INGREDIENTS: DIAZOLIDINYL UREA; EDETATE DISODIUM; GLYCERIN; C12-15 PARETH-9; water; TROLAMINE

Xpect Extra Strength Itch Relief

Active ingredients

Diphenhydramine hydrochloride 2%

Purpose

External Analgesic

Uses

for temporary relief of pain and itching associated with minor skin irritations and rashes due to insect bites, poison oak and poison sumac

Warnings

For external use only

Do not use

- on large areas of the body

- with any other product containing diphenhydramine hydrochloride, even one taken by mouth

Ask a doctor before use

- on chicken pox

- on measles

When using this produt

- avoid contact with the eyes

Stop use and ask a doctor if

- condition worsens symptoms persist more than 7 days or clear up and occur again within a few days

Keep out of reach of children.

If swallowed, get medical help or contact a Poison Control Center right away.

Directions

- do not use more than directed
- adults & children 12 years and over: apply to affected area not more than 3 to 4 times daily
- children under 12: consult a doctor

Other information

- store at room temperature

Inactive Ingredients

germaben II, edetate disodium, glycerin, tomadol 25-9, purified water, triethanolamine

Questions?

1-877-973-2811 M-F 8am-5pm

Package Principal Display Panel

Extra Strength

ITCH RELIEF

Quick Itch & Pain Relief

Diphenhydramine HCl 2%

Convenient pump spray allows no-touch application. Use as a first aid treatment for insect bites and rashes from poison ivy, oak & sumac.

2 fl. oz. (59.1 mL)

Xpect® First aid